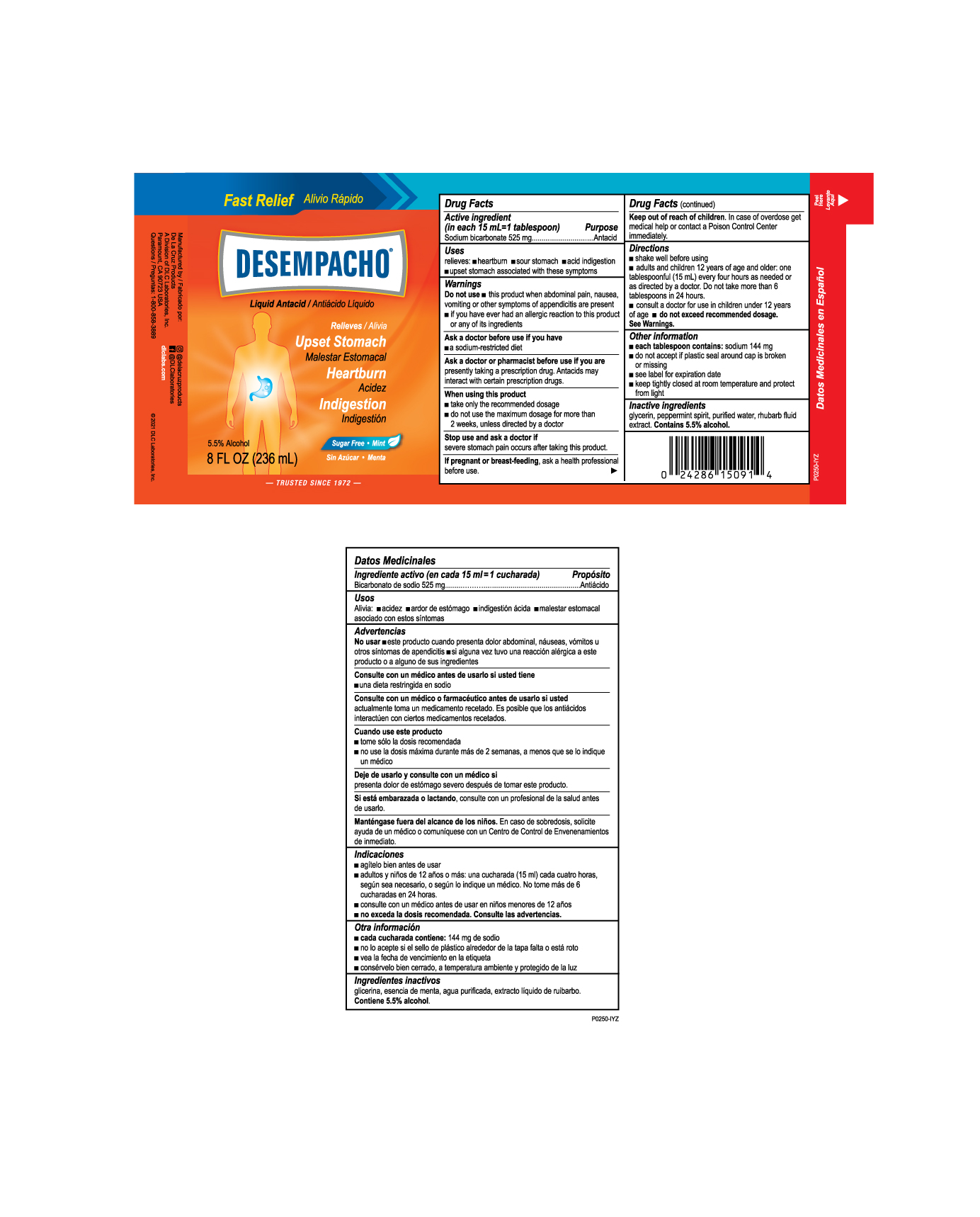 DRUG LABEL: De La Cruz Desempacho
NDC: 24286-1523 | Form: LIQUID
Manufacturer: DLC LABORATORIES, INC.
Category: otc | Type: HUMAN OTC DRUG LABEL
Date: 20260107

ACTIVE INGREDIENTS: SODIUM BICARBONATE 525 mg/15 mL
INACTIVE INGREDIENTS: PEPPERMINT; WATER; RHUBARB; GLYCERIN; ALCOHOL

DE LA CRUZ® DESEMPACHO® LIQUID

Drug Facts

Active ingredient (in each 15 mL=1 tablespoon)

Sodium bicarbonate 525 mg

Purpose

Antacid

Uses

relieves:

- heartburn
- sour stomach
- acid indigestion
- upset stomach associated with these symptoms

Warnings

Do not use

- this product when abdominal pain, nausea, vomiting or other symptoms of appendicitis are present
- if you have ever had an allergic reaction to this product or any of its ingredients

Ask a doctor before use if you have

- a sodium-restricted diet

Ask a doctor or pharmacist before use if you are presently taking a prescription drug. Antacids may interact with certain prescription drugs.

When using this product

- take only the recommended dosage
- do not use the maximum dosage for more than 2 weeks, unless directed by a doctor

Stop use and ask a doctor if severe stomach pain occurs after taking this product.

PREGNANCY OR BREAST FEEDING

If pregnant or breast-feeding, ask a health professional before use.

Keep out of reach of children. In case of overdose get medical help or contact a Poison Control Center immediately.

Directions

- shake well before using
- adults and children 12 years of age and older: one tablespoonful (15 mL) every four hours as needed or as directed by a doctor. Do not take more than 6 tablespoons in 24 hours.
- consult a doctor for use in children under 12 years of age
- do not exceed recommended dosage. See Warnings.

Other information

- each tablespoon contains: sodium 144 mg
- do not accept if plastic seal around cap is broken or missing
- see label for expiration date
- keep tightly closed at room temperature and protect from light

Inactive ingredients

glycerin, peppermint spirit, purified water, rhubarb fluid extract. Contains 5.5% alcohol.

Questions

1-800-858-3889

@delacruzproducts

@DLClaboratories
dlclabs.com

©2021 DLC Laboratories, Inc.

Manufactured by:
De La Cruz Products
A Division of DLC Laboratories, Inc.
Paramount, CA 90723 USA

PRINCIPAL DISPLAY PANEL - 236 mL Bottle Label

Fast Relief

DESEMPACHO®

Liquid Antacid

Relieves

Upset Stomach

Heartburn

Indigestion

Sugar Free • mint

5.5% Alcohol

8 FL OZ (236 mL)

Trusted since 1972